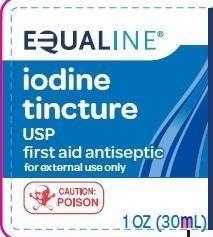 DRUG LABEL: Iodine
NDC: 41163-088 | Form: LIQUID
Manufacturer: United Natural Foods, Inc. dba UNFI
Category: otc | Type: HUMAN OTC DRUG LABEL
Date: 20260216

ACTIVE INGREDIENTS: IODINE 20 mg/1 mL
INACTIVE INGREDIENTS: ALCOHOL; WATER; SODIUM IODIDE

Equaline 088.000/088AA
Iodine Tincture U.S.P.

Active Ingredient

Iodine tincture U.S.P. 100% (2% iodine)

Purpose

First aid antiseptic

Use

First aid to help prevent skin infection in

- minor cuts
- scrapes
- burns

Warnings

For external use only

Ask a doctor before use if you have

deep or puncture wounds, animal bites or serious burns

When using this product

- do not use in eyes or apply over large areas of the body
- do not use longer than 1 week unless directed by a doctor

Stop use and ask a doctor if

condition persists or gets worse

Keep out of reach of children.

If swallowed, get medical help or contact a Poison Control Center right away.

Directions

- clean the affected area
- apply a small amount on the area 1 to 3 times daily
- may be covered with a sterile bandage
- if bandaged, let dry first

Inactive ingredients

Not Listed: alcohol (47% v/v), purified water, sodium iodide

Other information

Product will stain skin and clothing

Distributed by UNFI, Eden Prairie, MN 55344 USA

Contact us at 1-877-932-7948 or www.supervalu-ourownbrands.com

Principal display panel

NDC 41163-088-10

EQUALINE

iodine tincture USP

first aid antiseptic

for external use only

CAUTION POISON

1 OZ (30 mL)